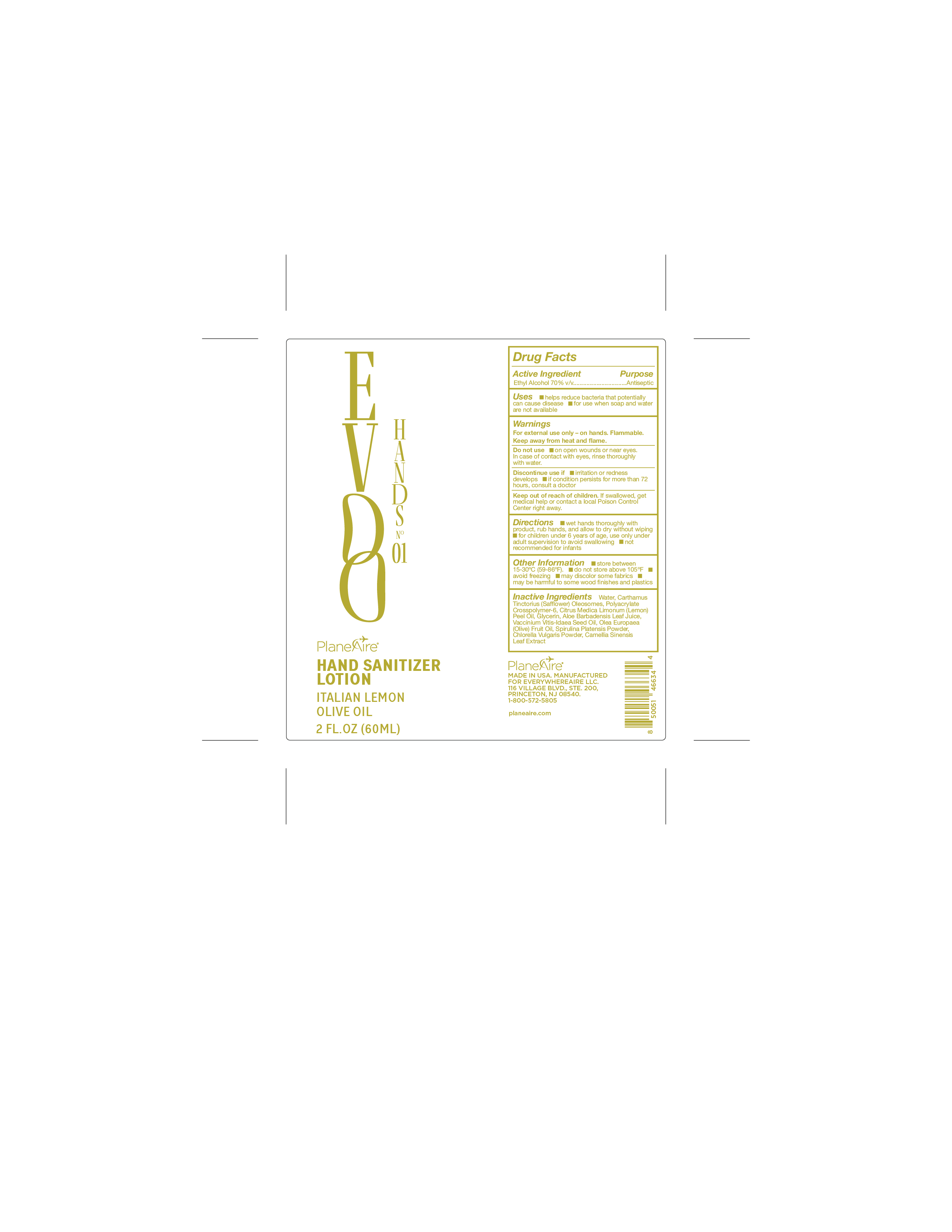 DRUG LABEL: PlaneAire Hands Lemon Olive Oil Hand Sanitizer
NDC: 80335-119 | Form: LOTION
Manufacturer: EverywhereAire LLC
Category: otc | Type: HUMAN OTC DRUG LABEL
Date: 20251106

ACTIVE INGREDIENTS: ALCOHOL 70 mL/100 mL
INACTIVE INGREDIENTS: OLEA EUROPAEA FRUIT VOLATILE OIL; CAMELLIA SINENSIS LEAF; GLYCERIN; LEMON OIL; CARTHAMUS TINCTORIUS (SAFFLOWER) OLEOSOMES; SPIRULINA PLATENSIS; CHLORELLA VULGARIS; POLYACRYLATE CROSSPOLYMER-6; WATER; VACCINIUM VITIS-IDAEA SEED OIL; ALOE BARBADENSIS LEAF JUICE

PlaneAire Hands Lemon Olive Oil Hand Sanitizer

Active Ingredient

Ethyl Alcohol 70% v/v

Uses

- helps reduce bacteria that potentially can cause disease
- for use when soap and water are not available

Purpose

Antiseptic

WARNINGS

For external use only- on hands.

Flammable. Keep away from heat and flame.

Do not use

on open wounds or near eyes

In case of contact with eyes, rinse thoroughly with water

Discontinue use if

- irritation or redness develops
- if condition persists for more than 72 hours, consult a doctor

Keep out of reach of children

If swallowed, get medical help or contact a local Poison Control Center right away

Directions

- wet hands thoroughly with product, rub hands, and allow to dry without wiping
- for children under 6 years of age, use only under adult supervision to avoid swallowing
- not recommended for infants

Other Information

- store between 15-30 C (59-86 F)
- do not store above 105 F
- avoid freezing
- may discolor some fabrics
- may be harmful to some wood finishes and plastics

Inactive Ingredients

Water, Carthamus Tinctorius (Safflower) Oleosomes, Polyacrylate Crosspolymer-6, Citrus Medica Limonum (Lemon) Peel Oil, (-) Glycerin, Aloe Barbadensis Leaf Juice, Vaccinium Vitis-Idaea Seed Oil, Olea Europaea (Olive) Fruit Oil, Spirulina Platensis Powder, Chlorella Vulgaris Powder, Camellia Sinensis Leaf Extract

Indications and Usage Dosage and Administration

title of section updated

title of section updated